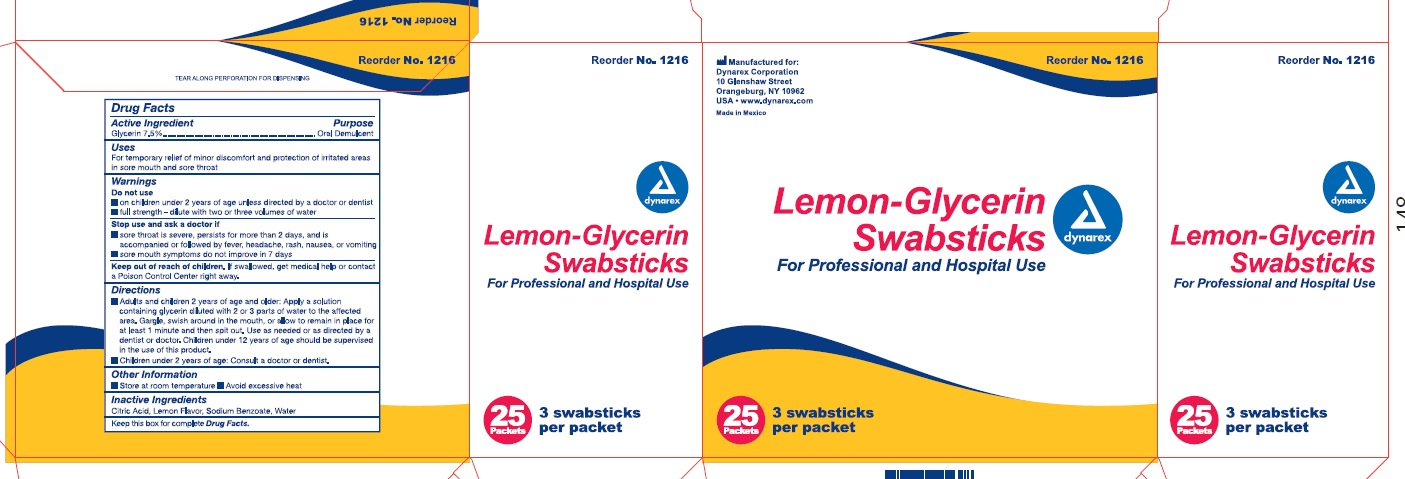 DRUG LABEL: Lemon Glycerin
NDC: 67777-161 | Form: SWAB
Manufacturer: Dynarex Corporation
Category: otc | Type: HUMAN OTC DRUG LABEL
Date: 20251218

ACTIVE INGREDIENTS: GLYCERIN 0.3 g/4 g
INACTIVE INGREDIENTS: CITRIC ACID MONOHYDRATE; WATER; SODIUM BENZOATE

1216 Lemon Glycerin Swabsticks NDC 67777-161-10

Active Ingredient

Glycerin 7.5% v/v

Purpose

Oral Demulcent

Uses

- For temporary relief of minor discomfort and protection or irritated areas in sore mouth and sore throat
- Dry mouth relief

Warnings

For Oral Use Only

Do not get in eyes

KEEP OUT OF REACH OF CHILDREN

Directions

- Swab mouth as needed.
- Discard after single use.
- Children under the age of 12 should be supervised in the use of this product.
- Children under 2 years of age consult a doctor.

Other information

- Store at room temperature. 15° - 30°C (59°-86°F)
- Avoid excessive heat.

Inactive Ingredients:

Citric acid, lemon flavor, sodium benzoate, water

Principle Display Panel

NDC 67777-161-10

Lemon - Glycerin Swabsticks

For Professional and Hospital Use.

25 Packets

3 swabsticks per packet